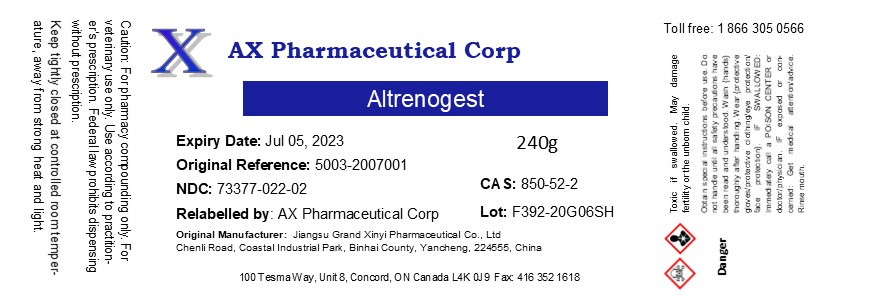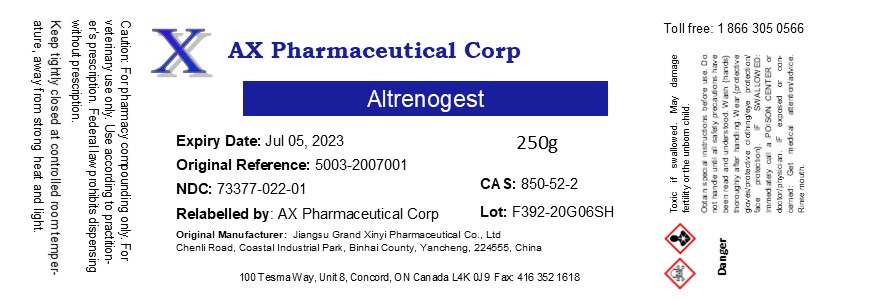 DRUG LABEL: Altrenogest
NDC: 73377-022 | Form: POWDER
Manufacturer: AX Pharmaceutical Corp
Category: other | Type: BULK INGREDIENT - ANIMAL DRUG
Date: 20230929

ACTIVE INGREDIENTS: ALTRENOGEST 1 g/1 g

Altrenogest